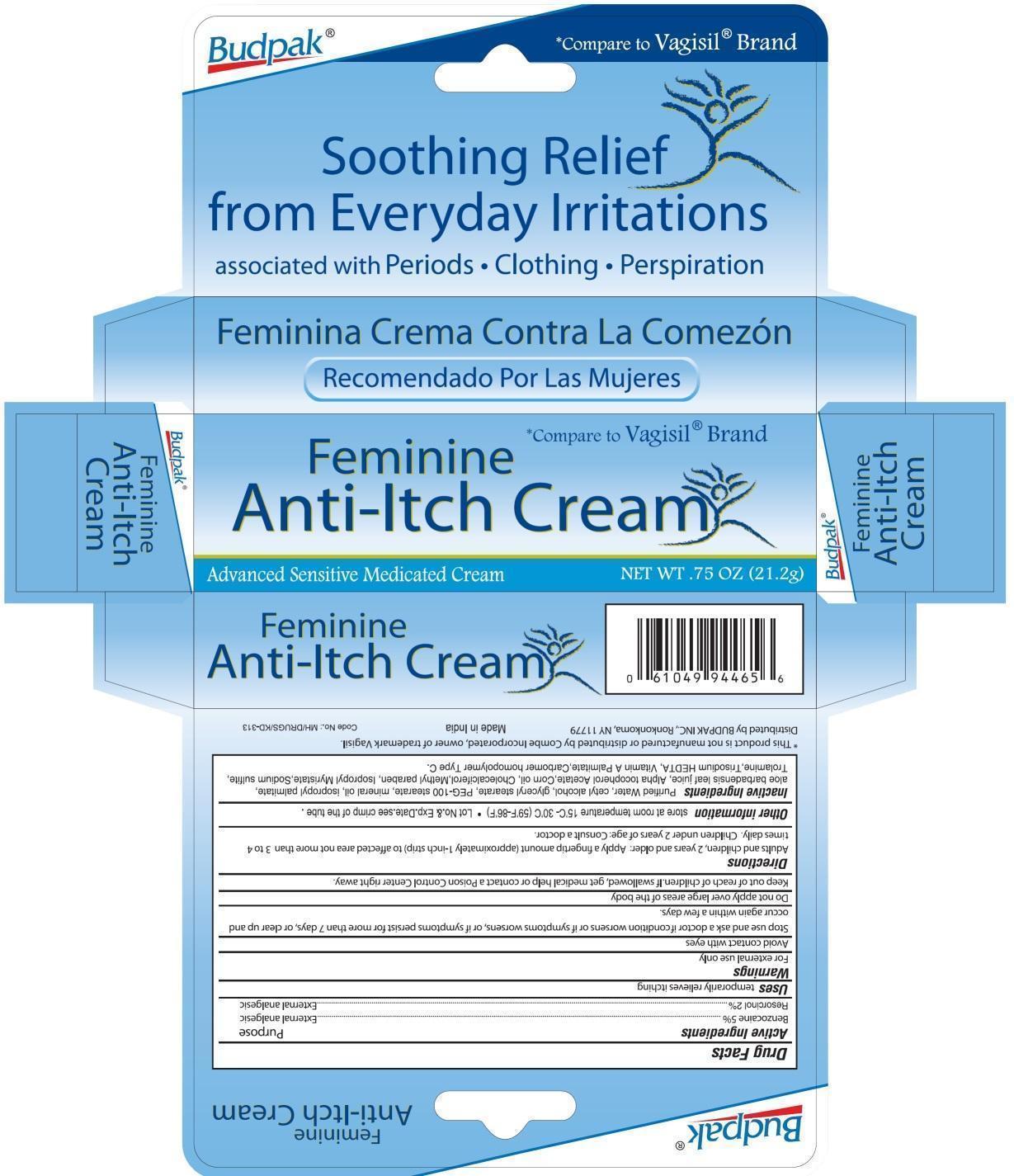 DRUG LABEL: Budpak Feminine Anti-Itch
NDC: 27293-022 | Form: CREAM
Manufacturer: Budpak Inc.
Category: otc | Type: HUMAN OTC DRUG LABEL
Date: 20130608

ACTIVE INGREDIENTS: BENZOCAINE 0.05 g/1 g; RESORCINOL 0.02 g/1 g
INACTIVE INGREDIENTS: WATER; CETYL ALCOHOL; GLYCERYL MONOSTEARATE; PEG-100 STEARATE; MINERAL OIL; ISOPROPYL PALMITATE; ALOE VERA LEAF; .ALPHA.-TOCOPHEROL ACETATE; CORN OIL; CHOLECALCIFEROL; METHYLPARABEN; ISOPROPYL MYRISTATE; SODIUM SULFITE; TROLAMINE; TRISODIUM HEDTA; VITAMIN A PALMITATE; CARBOMER HOMOPOLYMER TYPE C

Active Ingredients

Benzocaine 5%

Resorcinol 2%

Purpose

External analgesic

Uses

- temporarily relieves itching

Warnings

For external use only

Avoid contact with eyes

Stop use and ask a doctor if condition worsens or if symptoms worsens, or if symptoms persist for more than 7 days, or clear up and occur again within a few days.

Do not apply over large areas of the body.

Keep out of reach of children. If swallowed, get medical help or contact a Poison Control Center right away

Directions

Adults and children, 2 years and older:

- Apply a fingertip amount (approximately 1-inch strip) to affected area not more than 3 to 4 times daily.

Children under 2 years of age: Consult a doctor

Other information

- Store at room temperature 15°C to 30°C (59°F to 86°F).
- Lot No. Exp. Date: see crimp of the tube.

Inactive Ingredients

Purified water, cetyl alcohol, glyceryl stearate, PEG-100 stearate, mineral oil, isopropyl palmitate, aloe barbadensis leaf juice, alpha tocopherol acetate, corn oil, cholecalciferol, methyl paraben, isopropyl myristate, sodium sulfite, trolamine, trisodium HEDTA, vitamin A palmitate, carbomer homopolymer type c.

PRINCIPAL DISPLAY PANEL

Budpak Feminine Anti-Itch Cream

Benzocaine 5%

Resorcinol 2%

External analgesic

NET WT 0.75 OZ (21.2 g)